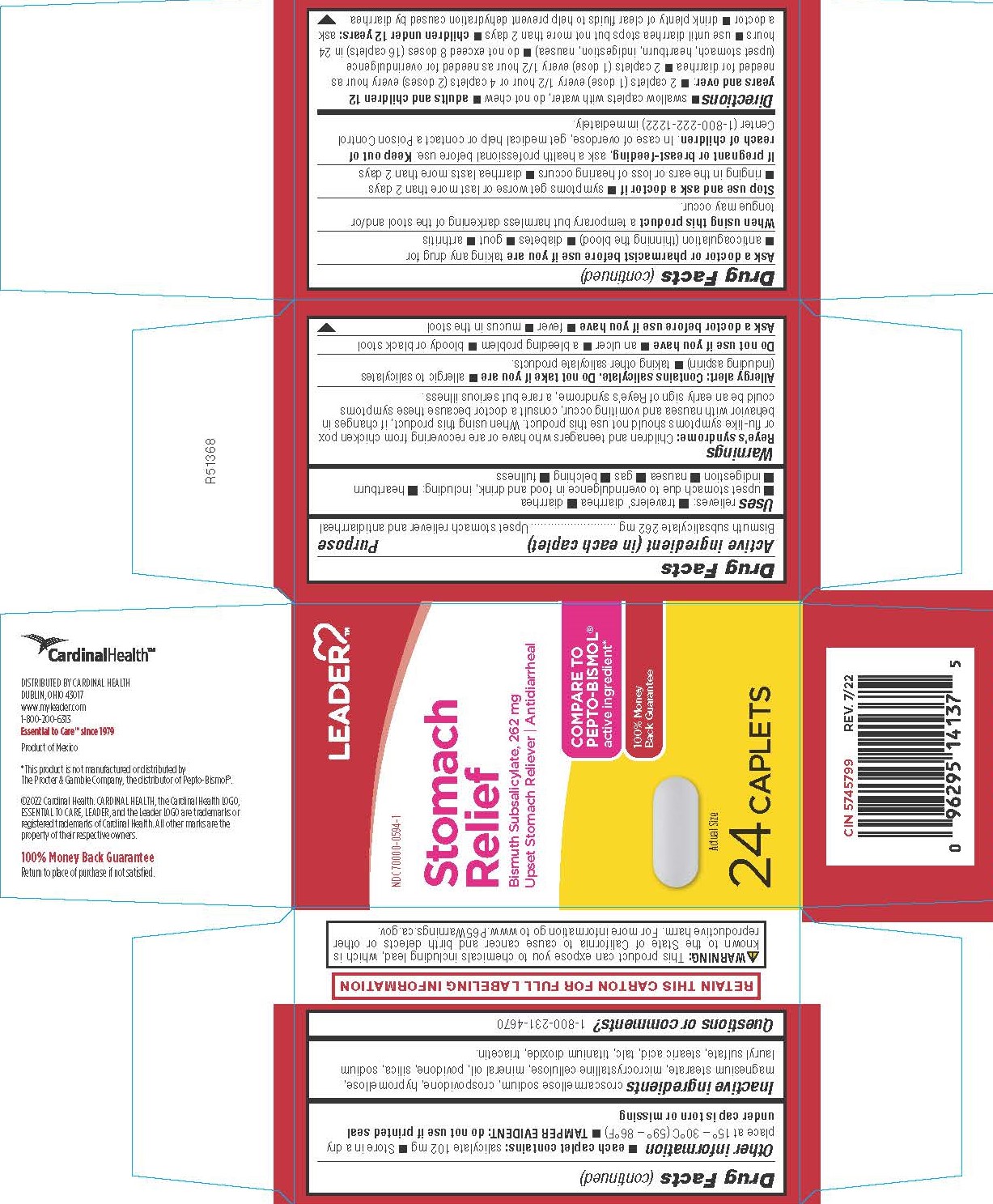 DRUG LABEL: Bismuth Subsalicylate
NDC: 70000-0594 | Form: TABLET, FILM COATED
Manufacturer: LEADER/ Cardinal Health 110, Inc.
Category: otc | Type: HUMAN OTC DRUG LABEL
Date: 20250211

ACTIVE INGREDIENTS: BISMUTH SUBSALICYLATE 262 mg/1 1
INACTIVE INGREDIENTS: CROSPOVIDONE; MICROCRYSTALLINE CELLULOSE; TALC; SODIUM LAURYL SULFATE; SILICON DIOXIDE; TITANIUM DIOXIDE; HYPROMELLOSES; CROSCARMELLOSE SODIUM; TRIACETIN; LIGHT MINERAL OIL; POVIDONE K30; STEARIC ACID; MAGNESIUM STEARATE

5346 - Cardinal

Drug Facts

Active ingredient (in each caplet)
Bismuth subsalicylate 262 mg

Purpose
Upset stomach reliever and antidiarrheal

Uses

relieves: ■ travelers’ diarrhea ■ diarrhea
■ upset stomach due to overindulgence in food and drink, including: ■ heartburn ■ indigestion ■ nausea ■ gas ■ belching ■ fullness

WARNINGS

Reye’s syndrome: Children and teenagers who have or are recovering from chicken pox or flu-like symptoms should not use this product. When using this product, if changes in behavior with nausea and vomiting occur, consult a doctor because these symptoms could be an early sign of Reye’s syndrome, a rare but serious illness.

Allergy alert: Contains salicylate. Do not take if you are

- allergic to salicylates (including aspirin)
- taking other salicylate products.

Do not use if you have

- an ulcer
- a bleeding problem
- bloody or black stool

Ask a doctor before use if you have

- fever
- mucus in the stool

Ask a doctor or pharmacist before use if you are taking any drug for

- anticoagulation (thinning the blood)
- diabetes
- gout
- arthritis

When using this product a temporary but harmless darkening of the stool and/or tongue may occur.

Stop use and ask a doctor if

- symptoms get worse or last more than 2 days
- ringing in the ears or loss of hearing occurs
- diarrhea lasts more than 2 days

PREGNANCY OR BREAST FEEDING

If pregnant or breast-feeding, ask a health professional before use.

Keep out of reach of children.

OVERDOSAGE

In case of overdose, get medical help or contact a Poison Control Center (1-800-222-1222) immediately.

Directions

- swallow caplets with water, do not chew

adults and children 12 years and over:

- 2 caplets (1 dose) every 1/2 hour or 4 caplets (2 doses) every hour as needed for diarrhea
- 2 caplets (1 dose) every 1/2 hour as needed for overindulgence (upset stomach, heartburn, indigestion, nausea)
- do not exceed 8 doses (16 caplets) in 24 hours
- use until diarrhea stops but not more than 2 days

children under 12 years: ask a doctor

- drink plenty of clear fluids to help prevent dehydration caused by diarrhea

Other information

- each caplet contains: salicylate 102 mg
- Store in a dry place at 15° – 30°C (59° – 86°F)
- TAMPER EVIDENT: do not use if printed seal under cap is torn or missing

INACTIVE INGREDIENT

croscarmellose sodium, crospovidone, hypromellose, magnesium stearate, microcrystalline cellulose, mineral oil, povidone, silica, sodium lauryl sulfate, stearic acid, talc, titanium dioxide, triacetin.

Questions or comments?

1-800-231-4670

RETAIN THIS CARTON FOR FULL LABELING INFORMATION

WARNING: This product can expose you to chemicals including lead, which is known to the State of California to cause cancer and birth defects or other reproductive harm. For more information go to www.P65Warnings.ca.gov.

COMPARE TO PEPTO-BISMOL active ingredient*

*This product is not manufactured or distributed by Procter & Gamble Inc., the distributor of Pepto-Bismol®.

DISTRIBUTED BY CARDINAL HEALTH
DUBLIN, OHIO 43017
www.myleader.com
1-800-200-6313
Essential to Care™ since 1979
Product of Mexico